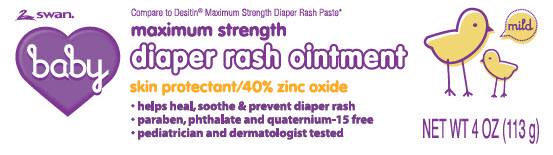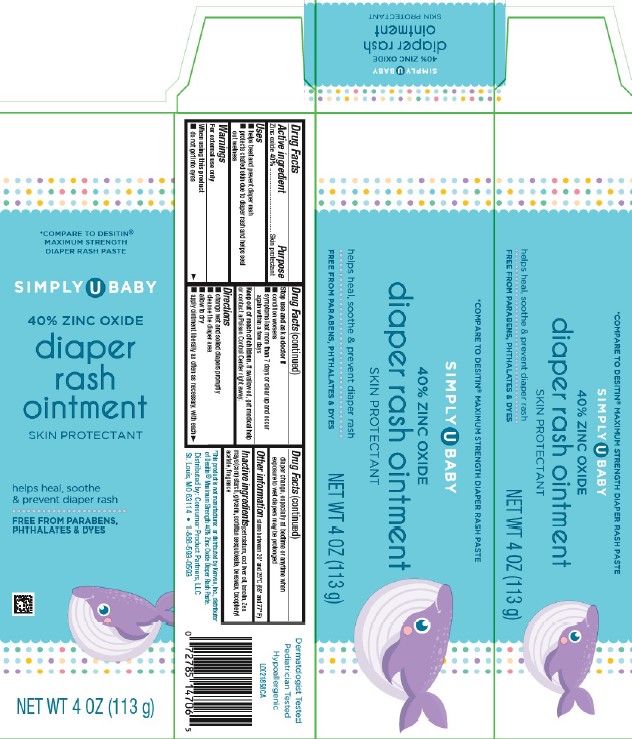 DRUG LABEL: Diaper Rash
NDC: 11344-020 | Form: PASTE
Manufacturer: Consumer Product Partners, LLC
Category: otc | Type: HUMAN OTC DRUG LABEL
Date: 20250324

ACTIVE INGREDIENTS: ZINC OXIDE 400 mg/1 g
INACTIVE INGREDIENTS: PETROLATUM; COD LIVER OIL; LANOLIN; STARCH, CORN; GLYCERIN; SORBITAN SESQUIOLEATE; YELLOW WAX; .ALPHA.-TOCOPHEROL ACETATE

Swan_Simply U 020.002/020AD
Diaper Rash Ointment 40% Zinc Oxide

Active ingredient

Zinc oxide 40%

Purpose

Skin protectant

Uses

- helps treat and prevent diaper rash
- protects chafed skin due to diaper rash and helps seal out wetness

Warnings

For external use only

When using this product

- do not get into eyes

Stop use and ask a doctor if

- condition worsens
- symptoms last more than 7 days or clear up and occur again within a few days

Keep out of reach of children.

If swallowed, get medical help or contact a Poison Control Center right away.

Directions

- change wet and soiled diapers promptly
- cleanse the diaper area
- allow to dry
- apply ointment liberally as often as necessary, with each diaper change, especially at bedtime or anytime when exposure to wet diapers may be prolonged

Other information

store between 20⁰ and 25⁰C (68⁰ and 77⁰F)

Inactive ingredients

petrolatum, cod liver oil, lanolin, Zea mays (corn) starch, glycerin, sorbitan sesquioleate, beeswax, tocopheryl acetate, fragrance

Disclaimer

*This product is not manufactured or distributed by Kenvue, Inc., distributor fo Desitin® Maximum Strength 40% Zinc Oxide Diaper Rash Paste.

Adverse reactions

Distributed by: Consumer Product Partners, LLC

St. Louis, MO 63114 1-888-593-0593

Dermatologist Tested

Pediatrician Tested

Hypoallergenic

Principal display panel

Swan baby

Compare to Desitin®Maximum Strength Diaper Rash Paste*

maximum strength

diaper rash ointment

skin protectant/40% zinc oxide

- helps heal, soothe, & prevent diaper rash
- paraben, phthalate and quaternium-15 free
- pediatrician and dermatologist tested

NET WT 4 OZ (113 g)

Principal display panel

*COMPARE TO DESITIN® MAXIMUM STRENGTH DIAPER RASH PASTE

SIMPLY U BABY

40% ZINC OXIDE

diaper rash ointment

SKIN PROTECTANT

helps heal, soothe, & prevent diaper rash

FREE FROM PARABENS, PHTHALATES & DYES

NET WT 4 OZ (113 g)